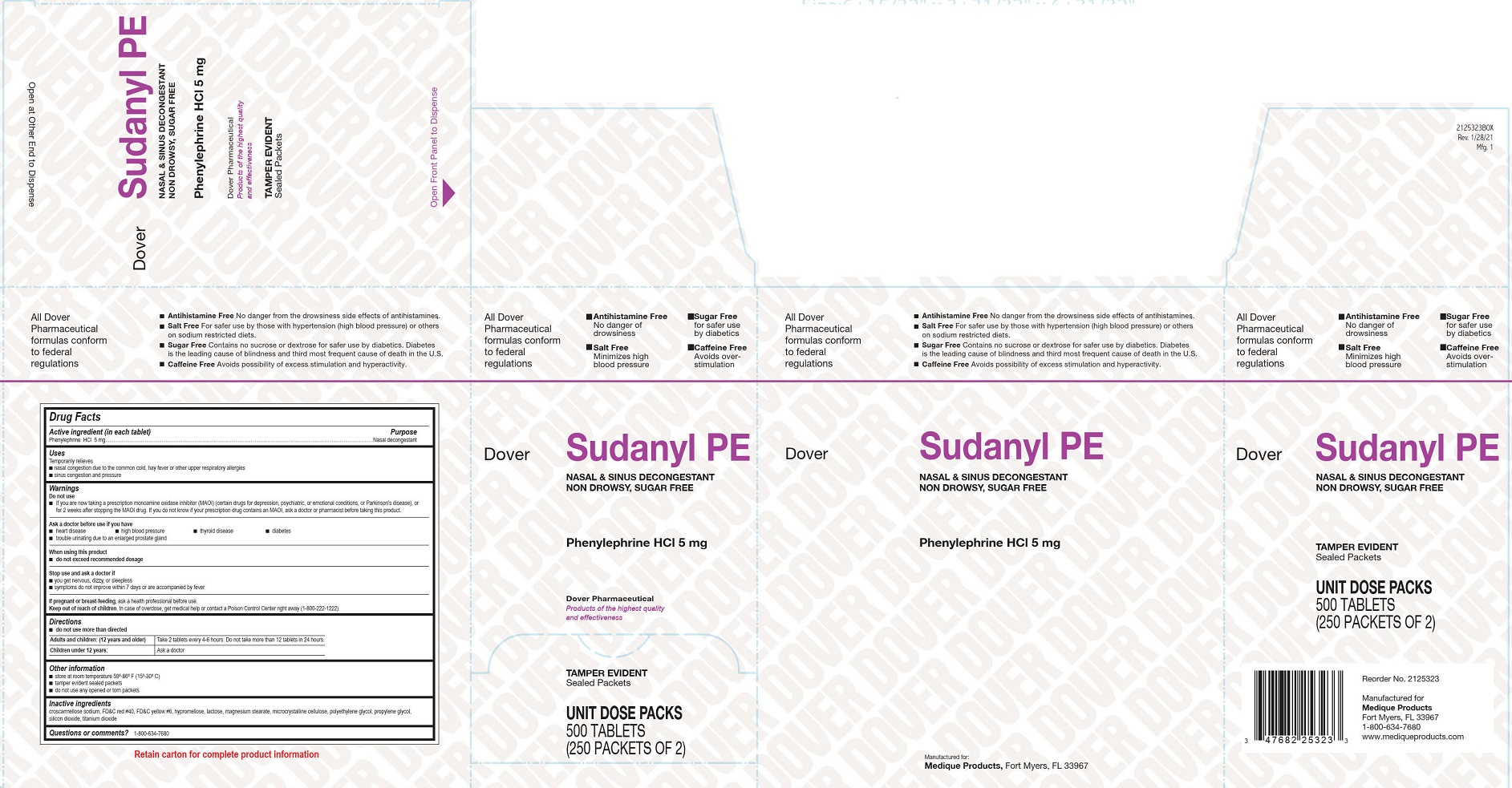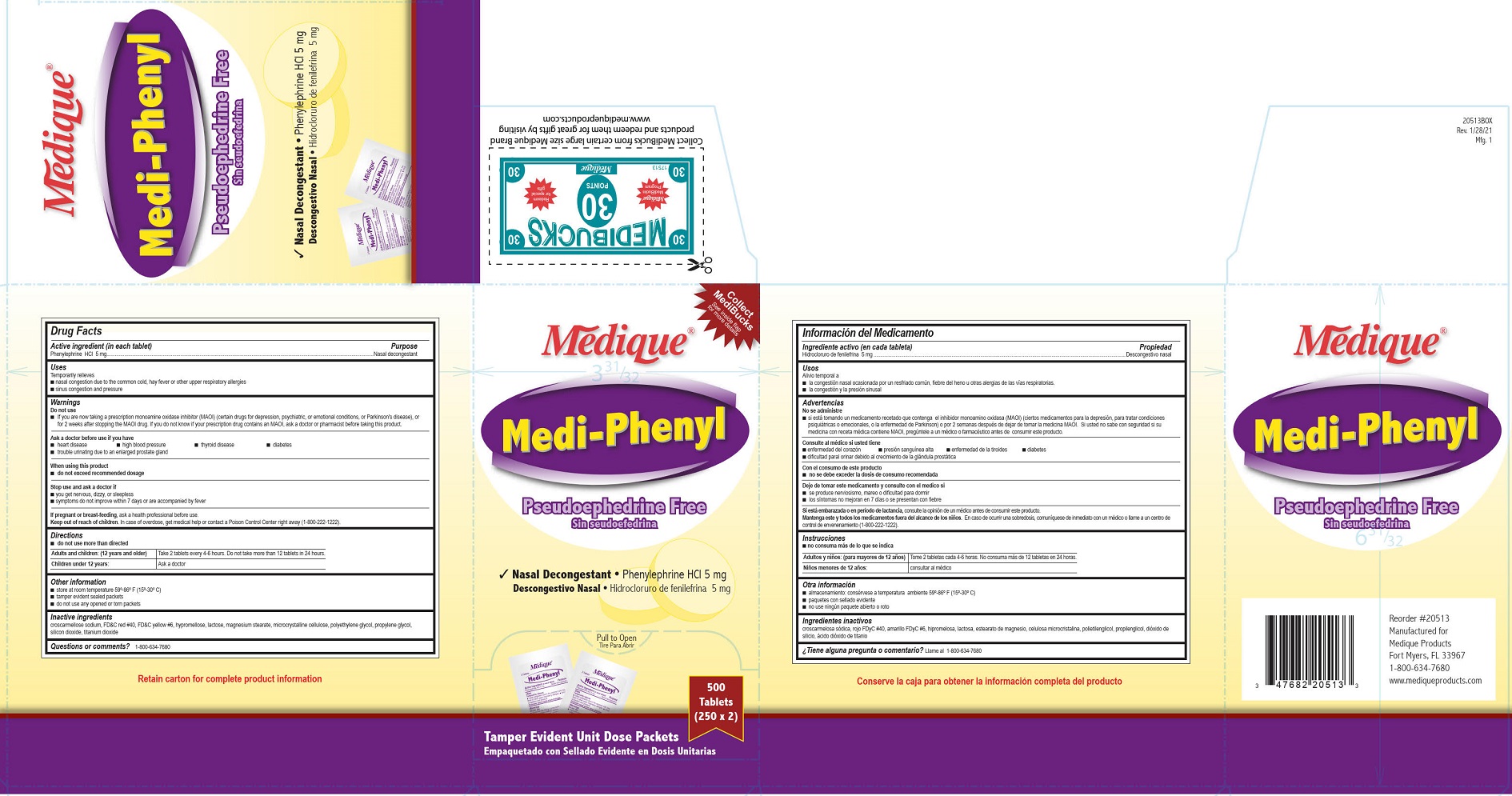 DRUG LABEL: Medique Medi-Phenyl
NDC: 47682-161 | Form: TABLET, FILM COATED
Manufacturer: Unifirst First Aid Corporation
Category: otc | Type: HUMAN OTC DRUG LABEL
Date: 20250908

ACTIVE INGREDIENTS: PHENYLEPHRINE HYDROCHLORIDE 5 mg/1 1
INACTIVE INGREDIENTS: CELLULOSE, MICROCRYSTALLINE; CROSCARMELLOSE SODIUM; FD&C RED NO. 40; FD&C YELLOW NO. 6; HYPROMELLOSES; LACTOSE; MAGNESIUM STEARATE; POLYETHYLENE GLYCOL, UNSPECIFIED; SILICON DIOXIDE; TITANIUM DIOXIDE; PROPYLENE GLYCOL

Medique and Dover Phenylephrine HCl 5mg

Drug Facts

Active ingredient (in each tablet)

Phenylephrine HCl 5mg

Purpose

Nasal decongestant

Uses

Temporarily relieves

■ nasal congestion due to the common cold, hay fever or other upper respiratory allergies

■ sinus congestion and pressure

Warnings

Do not use

- If you are now taking a prescription monoamine oxidase inhibitor (MAOI) (certain drugs for depression, psychiatric, or emotional conditions, or Parkinson's disease), or for 2 weeks after stopping the MAOI drug. If you do not know if your prescription drug contains an MAOI, ask a doctor or pharmacist before taking this product.

When using this product

■ do not exceed recommended dosage

Ask a doctor before use if you have

- heart disease
- high blood pressure
- thyroid disease
- diabetes
- trouble urinating due to an enlarged prostate gland

Stop use and ask a doctor if

■ you get nervous, dizzy, or sleepless

■ symptoms do not improve within 7 days or are accompanied by fever

PREGNANCY OR BREAST FEEDING

If pregnant or breast-feeding, ask a health professional before use.

Keep out of reach of children. In case of overdose, get medical help or contact a Poison Control Center right away (1-800-222-1222).

Directions

- do not use more than directed

DOSAGE AND ADMINISTRATION

Adults and children: (12 years and older)

Take 2 tablets every 4-6 hours. Do not take more than 12 tablets in 24 hours.

Children under 12 years:

Ask a doctor

Other information

- store at room temperature 59º-86º F (15º-30º C).
- tamper evident sealed packets.
- do not use any opened or torn packets

Inactive ingredients

croscarmellose sodium, FD&C red #40, FD&C yellow #6, hypromellose, lactose, magnesium stearate, microcrystalline cellulose, polyethylene glycol, propylene glycol, silicon dioxide, titanium dioxide

Questions or comments? 1-800-634-7680

205R Medique Medi-Phenyl Label

Medique®
Medi-Phenyl
Pseudoephedrine Free

Sin seudoefedrina

Nasal Decongestant • Phenylephrine HCl 5mg

Decongestivo Nasal • Hidrocloruro de fenilefrina 5 mg

Pull to Open

Tire Para Abrir

500 Tablets
(250 x 2)
Tamper Evident Unit Dose Packets

Empaquetado con Sellado Evidente en Dosis Unitarias

Dover Sudanyl Label

Dover Sudanyl PE
Nasal and Nasal Decongestant
Non-Drowsy, Sugar Free
Phenylephrine HCl 5mg
Dover Pharmaceutical
Products of the highest quality and effectiveness
Tamper Resistant
Sealed Packets
Unit Dose Packs
500 Tablets
(250 Packets of 2)